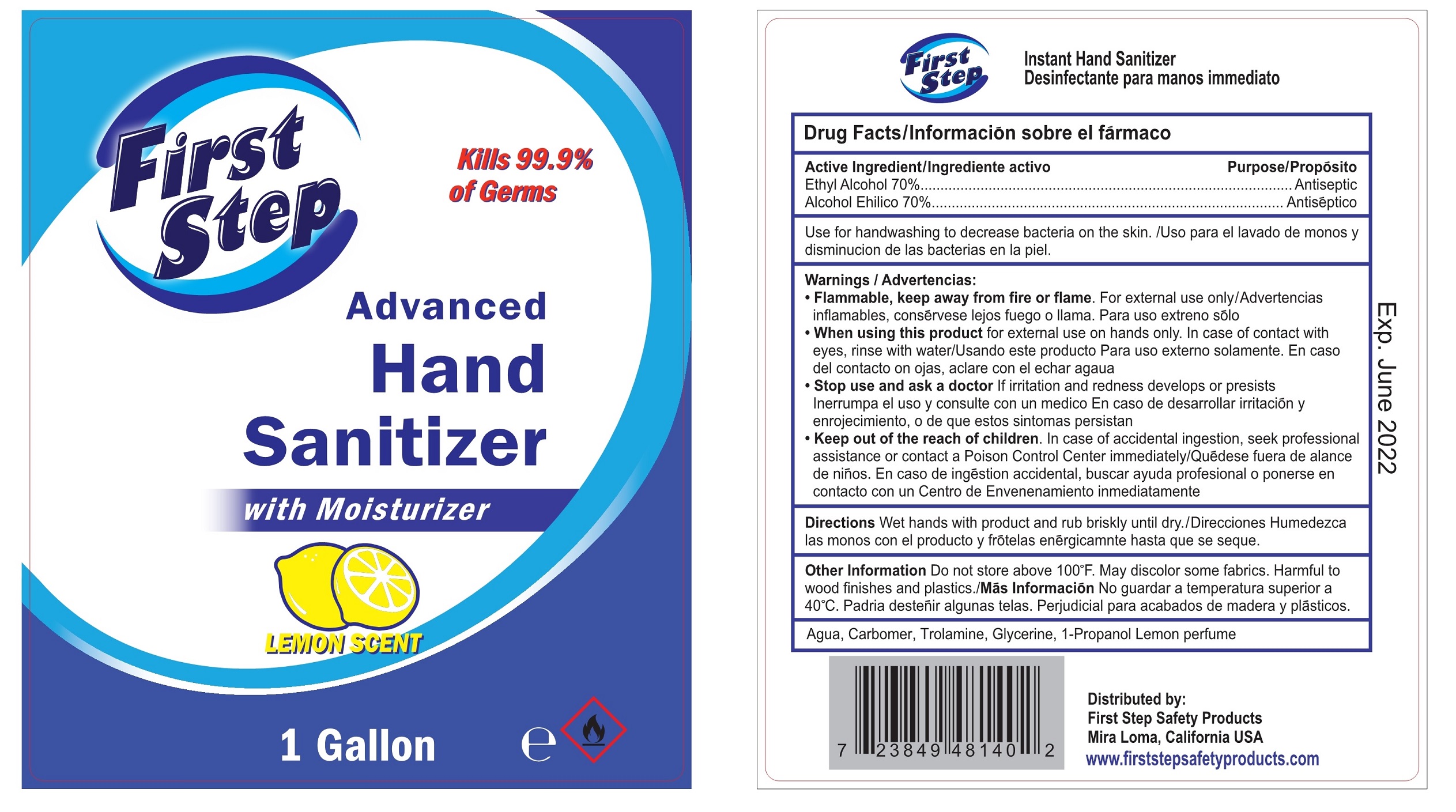 DRUG LABEL: Instant Hand Sanitizer
NDC: 79195-012 | Form: GEL
Manufacturer: First Step Safety Products Corporation
Category: otc | Type: HUMAN OTC DRUG LABEL
Date: 20200707

ACTIVE INGREDIENTS: ALCOHOL 2649.5 mL/3785 mL
INACTIVE INGREDIENTS: CARBOMER COPOLYMER TYPE A; TROLAMINE; GLYCERIN; WATER; LEMON

79195-012 1GALLON FIST STEP BY BETA

Active Ingredient(s)

Alcohol 70% v/v. Purpose: Antiseptic

Purpose

Antiseptic, Hand Sanitizer

Use for handwashing to decrease bacteria on the skin./Uso para el lavado de monos y disminucion de las bacterias en la piel.

Use

Hand Sanitizer to help reduce bacteria that potentially can cause disease. For use when soap and water are not available.

Warnings

- Flammable,keep away from fire or flame.For external use only/Advertencias inflamables,conservese lejos fuego o llama.Para uso extreno solo.
- When using this product for external use on hands only.In case of contact with eyes,rinse with water/Usando este producto Para uso externo solamente.En caso del contacto on ojas ,aclare con el echar agaua.
- Stop use and ask a doctor If irritation and redness develops or presists.Inerrumpa el uso y consulte con un medico En caso de desarrollar irritacion y enrojecimiento,o de que estos sintomas persistan.
- Keep out of the reach of children. In case of accidental ingestion,seek professional assistance or contact a Poison Control Center immediately/Quedese fuera de alance de ninos.En caso de ingestion accidental,buscar ayuda profesional o ponerse en contacto con un Centro de Envenenamiento inmediatamente.

Do not use

- in children less than 2 months of age
- on open skin wounds

When using this product keep out of eyes, ears, and mouth. In case of contact with eyes, rinse eyes thoroughly with water.
Stop use and ask a doctor if irritation or rash occurs. These may be signs of a serious condition.
Keep out of reach of children. If swallowed, get medical help or contact a Poison Control Center right away.

Stop use and ask a doctor if irritation or rash occurs. These may be signs of a serious condition.

Keep out of reach of children. If swallowed, get medical help or contact a Poison Control Center right away.

Directions

- Wet hands with product and rub briskly until dry./Direcciones Humedezca las monos con el producto y frotelas energicamnte hasta que se seque.

Other information

- Do not store above 100 F.May discolor some fabrics.Harmful to wood finishes and plastics./Mas Informacion No guardar a temperatura superior a 40 C.Padria destenir algunas telas.Perjudicial para acabados de madera y plasticos.

Inactive ingredients

WATER,CARBOMER COPOLYMER TYPE A,CARBOMER COPOLYMER TYPE A,CARBOMER COPOLYMER TYPE A,LEMON

Package Label - Principal Display Panel

1 Gallon in 1 bottle NDC: 79195-012-01